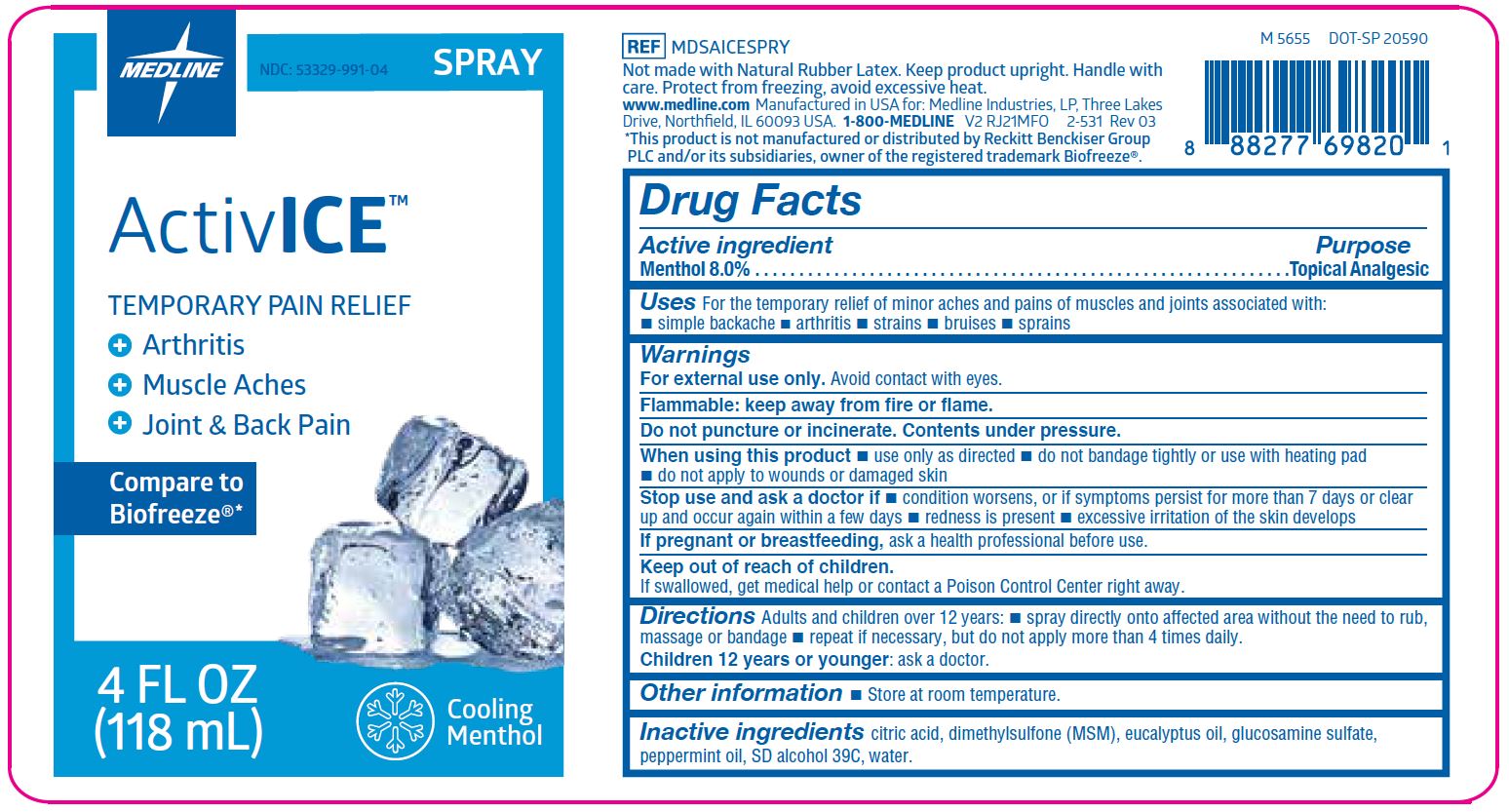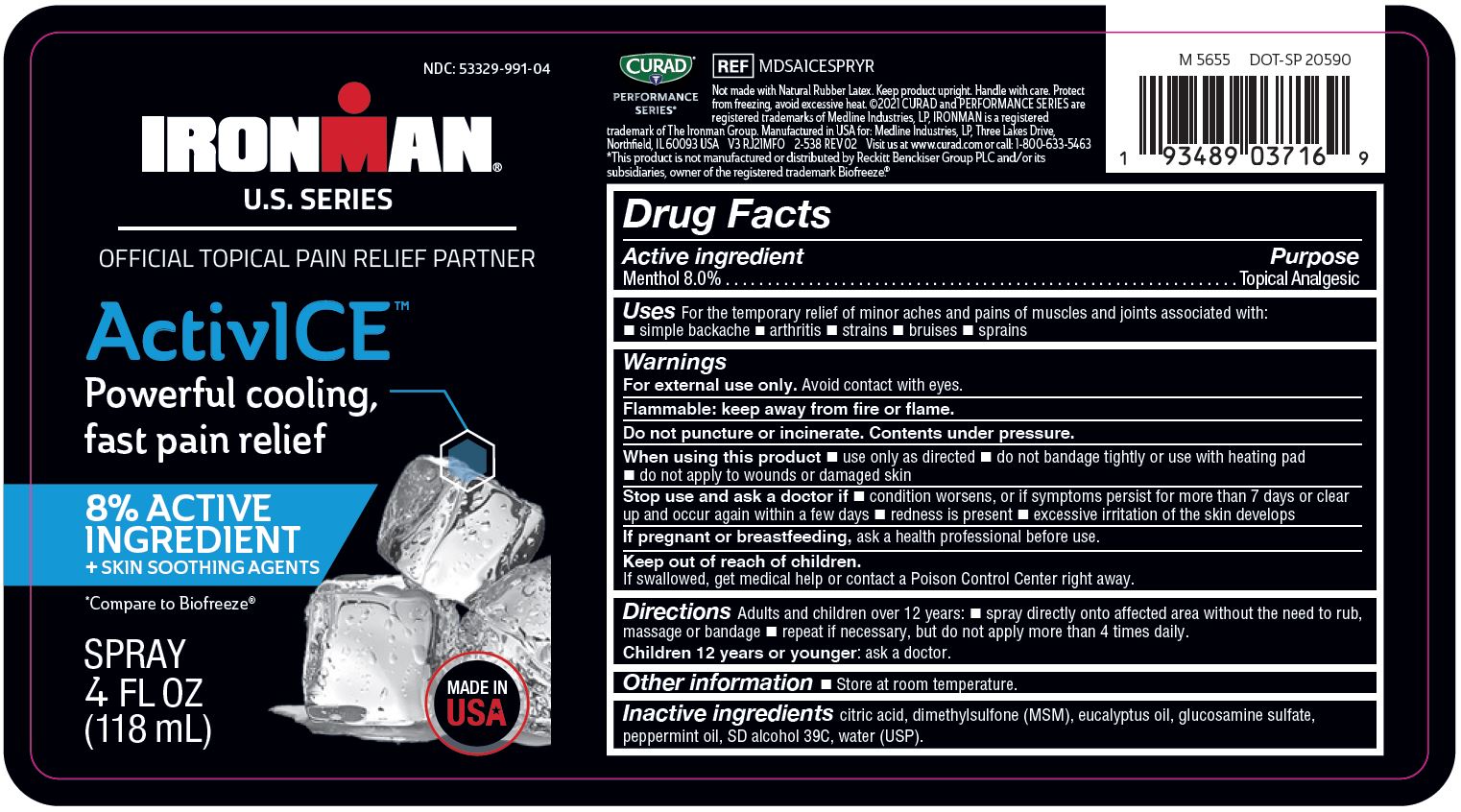 DRUG LABEL: ActivICE
NDC: 53329-991 | Form: SPRAY
Manufacturer: Medline Industries, LP
Category: otc | Type: HUMAN OTC DRUG LABEL
Date: 20241112

ACTIVE INGREDIENTS: MENTHOL 80 g/1000 g
INACTIVE INGREDIENTS: PEPPERMINT OIL; WATER; CITRIC ACID MONOHYDRATE; ALCOHOL; EUCALYPTUS OIL; DIMETHYL SULFONE; GLUCOSAMINE SULFATE

991 ActivICE spray

Active Ingredient

Menthol 8.0%

Purpose

Topical Analgesic

Uses

For the temporary relief of minor aches and pains of muscles and joints associated with:

- simple backache
- arthritis
- strains
- bruises
- sprains

Warnings

For external use only.

Avoid contact with eyes.

Flammable: keep away from fire or flame.

Do not puncture or incinerate. Contents under pressure.

When using this product

- use only as directed
- do not bandage tightly or use with heating pad
- do not apply to wounds or damaged skin

Stop use and ask a doctor if

- condition worsens, or if symptoms persist for more than 7 days or clear up and occur again within a few days
- redness is present
- excessive irritation of the skin develops

If pregnant or breastfeeding,

ask a health professional before use.

Keep out of reach of children.

If swallowed, get medical helop or contact a Poison Control Center right away.

Directions

Adults and children over 12 years:

- spray directly onto affected area without the need to rub, massage or bandage
- repeat if necessary, but do not apply more than 4 times daily.

Children 12 years or younger: ask a doctor.

Other Information

- Store at room temperature.

Inactive Ingredients

citric acid, dimethylsulfone (MSM), eucalyptus oil, glucosamine sulfate, peppermint oil, SD alcohol 39C, water.

Manufacturing Information

Manufactured for:
Medline Industries, LP
Three Lakes Drive, Northfield, IL 60093 USA
Made in USA
www.medline.com
1-800-MEDLINE (633-5463)
REF: MDSAICESPRY, V2 RJ21MFO

REF: MDSAICESPRYR, V2 RJ21MFO